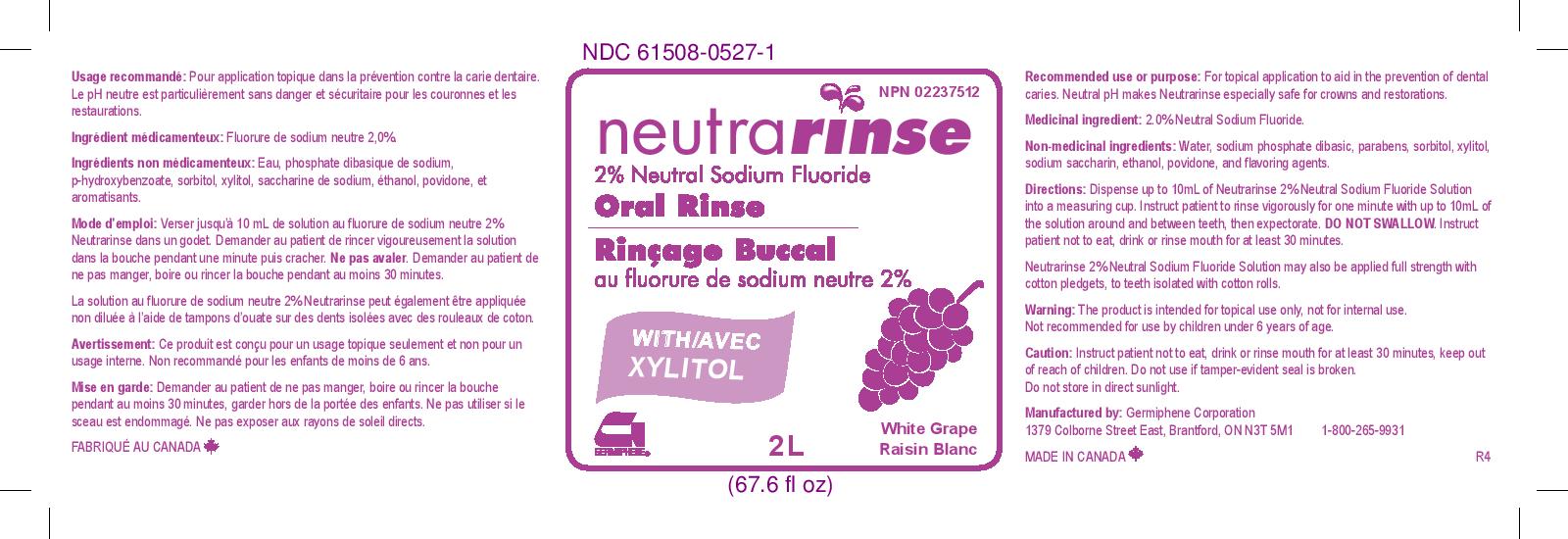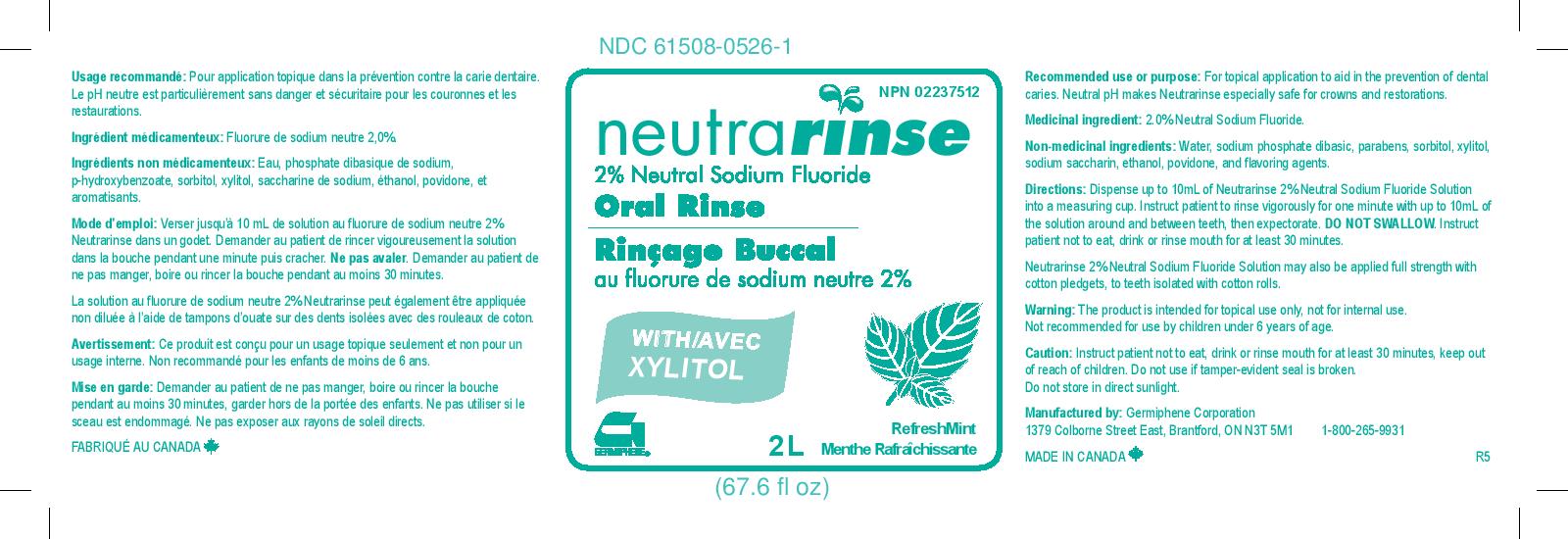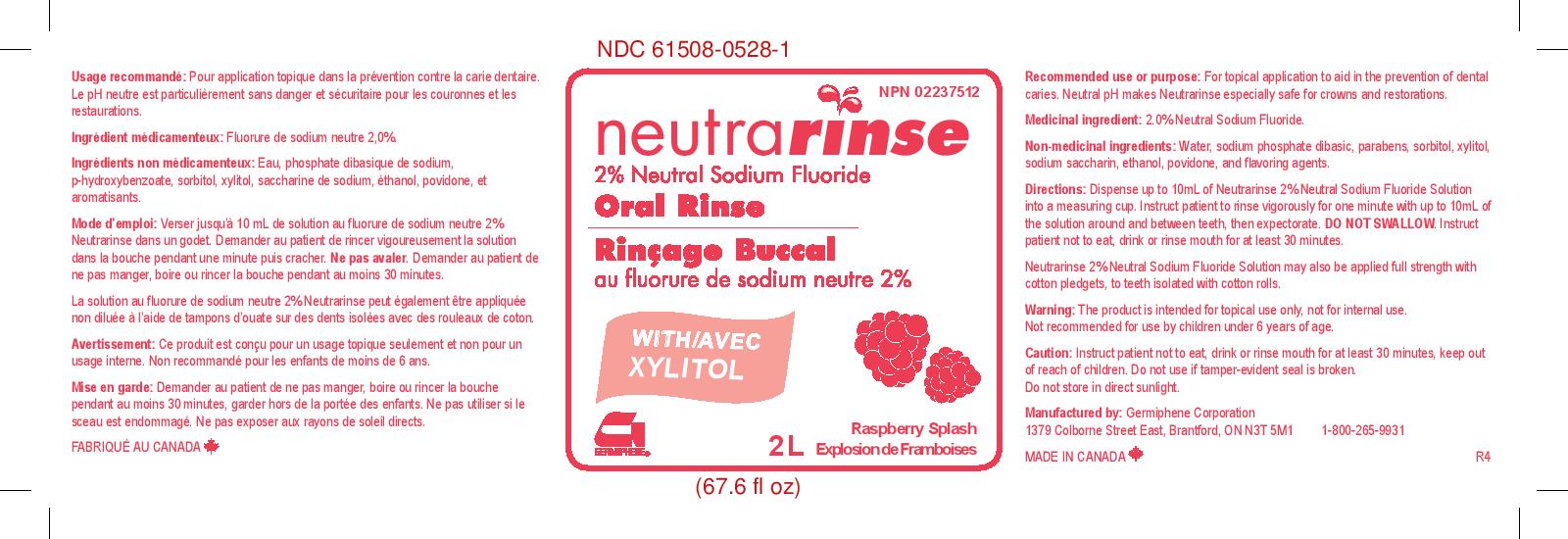 DRUG LABEL: Neutrarinse 2% Neutral Sodium Floride Oral Rinse White Grape
NDC: 61508-0527 | Form: RINSE
Manufacturer: Germiphene Corporation
Category: otc | Type: HUMAN OTC DRUG LABEL
Date: 20170203

ACTIVE INGREDIENTS: SODIUM FLUORIDE 2 g/100 g
INACTIVE INGREDIENTS: ALCOHOL 1 g/100 g; METHYLPARABEN 0.052 g/100 g; POVIDONE 0.3 g/100 g; SODIUM PHOSPHATE, DIBASIC 0.043 g/100 g; SORBITOL 15 g/100 g; WATER 76.4 g/100 g; XYLITOL 5 g/100 g; SACCHARIN SODIUM 0.01 g/100 g; PROPYLPARABEN 0.01 g/100 g

Neutrarinse

Recommended use:

For topical application to aid in the prevention of dental caries.

PURPOSE

Neutral pH makes Neutrarinse especially safe for crowns and restorations.

Medicinal ingredient:

2.0% Neutral sodium fluoride

Non-medicinal ingredients:

Water, sodium phosphate dibasic, parabens, sorbitol, xylitol, sodium saccharin, ethanol, povidone, and flavouring agents.

Directions:

Dispense up to 10 mL of Neutrarinse 2% Neutral Sodium Fluoride Solution into a measuring cup. Instruct patient to rinse vigorously for one minute with up to 10 mL of the solution arond and between teeth, then expectorate. DO NOT SWALLOW. Instruct patient not to eat, drink, or rinse mouth for at least 30 minutes.

Neutrarinse 2% Neutral Sodium Fluoride Solution may also be applied full strength with cotton pledgets, to teeth isolated with cotton rolls.

Warning:

The product is intended for topical use only, not for internal use. Not recommended for use by children under 6 years of age.

Instruct patient not to eat, drink, or rinse mouth for at least 30 minutes. Do not use if tamper-evident seal is broken. Do not store in direct sunlight.

Keep out of reach of children.